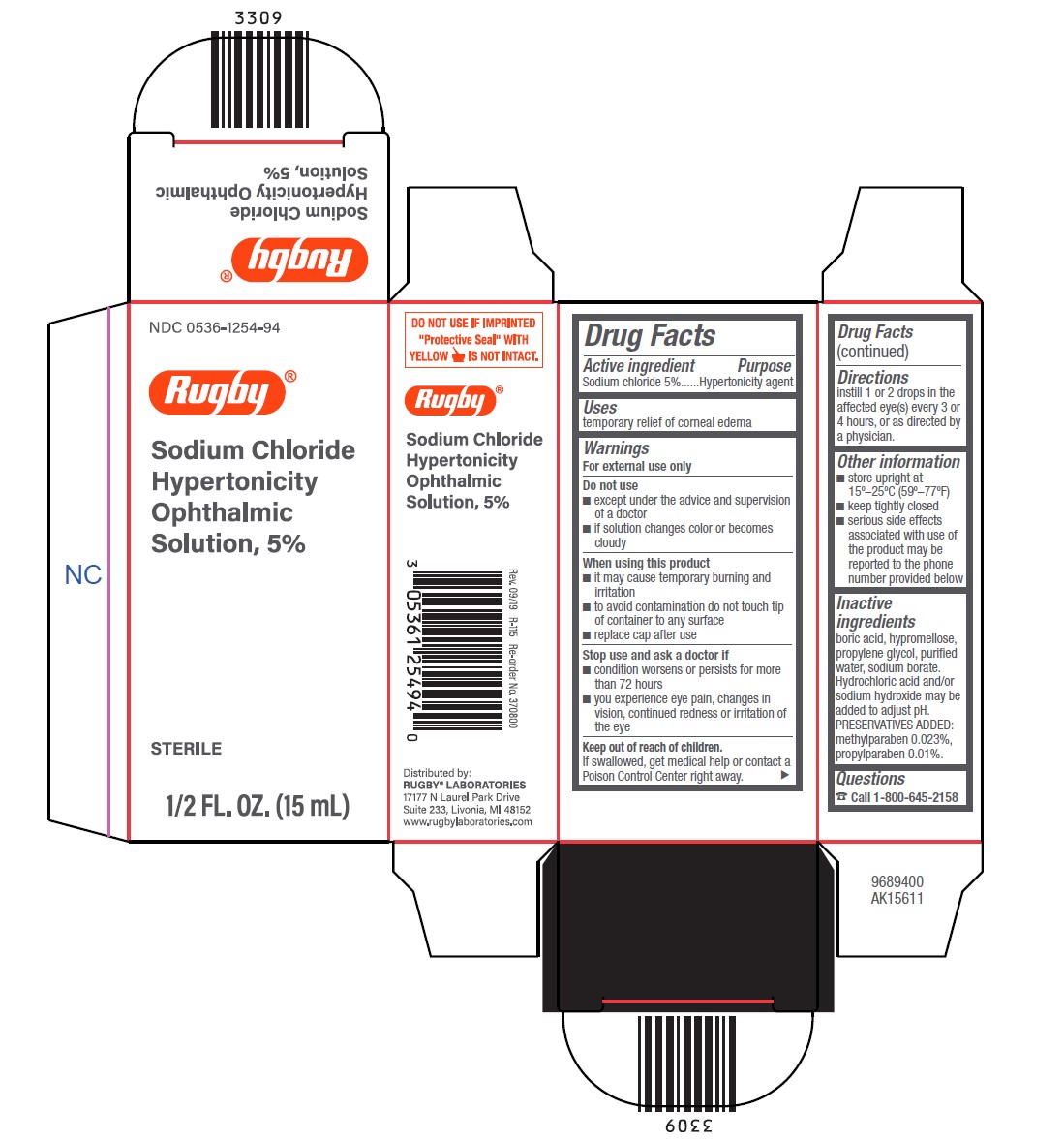 DRUG LABEL: Sodium Chlorode Hypertonicity Ophthalmic Solution
NDC: 0536-1254 | Form: SOLUTION
Manufacturer: Rugby Laboratories
Category: otc | Type: HUMAN OTC DRUG LABEL
Date: 20240920

ACTIVE INGREDIENTS: SODIUM CHLORIDE 50 mg/1 mL
INACTIVE INGREDIENTS: BORIC ACID; HYPROMELLOSE 2208 (100 MPA.S); PROPYLENE GLYCOL; WATER; SODIUM BORATE; METHYLPARABEN; PROPYLPARABEN; HYDROCHLORIC ACID; SODIUM HYDROXIDE

Active ingredients

Sodium chloride 5%

Purpose

Hypertonicity agent

Uses

temporary relief of corneal edema

Warnings

Do not use

- except under the advice and supervision of a doctor
- if solution changes color or becomes cloudy

When using this product

- it may cause temporary burning and irritation
- to avoid contamination do not touch tip of container to any surface
- replace cap after use

Stop use and ask a doctor if

- condition worsens or persists for more than 72 hours
- you experience eye pain, changes in vision, continued redness or irritation of the eye

Keep out of reach of children.

If swallowed, get medical help or contact a Poison Control Center right away.

Directions

- instill 1 or 2 drops in the affected eye(s) every 3 or 4 hours, or as directed by a physician.

Other information

- store upright at 15° - 25°C (59° - 77°F)
- keep tightly closed
- serious side effects associated with use of the product may be reported to the phone number provided below

Inactive ingredients

boric acid, hypromellose, propylene glycol, purified water, sodium borate. Hydrochloric acid and/or sodium hydroxide may be added to adjust pH. PRESERVATIVES ADDED: methylparaben 0.023%, propylparaben 0.01%.

Questions?

[phone icon] Call 1-800-645-2158

Package/Label Principal Display Panel – carton

NDC 0536-1254-94

Rugby®

Sodium Chloride
Hypertonicity
Ophthalmic
Solution, 5%

STERILE

1/2 FL. OZ. (15 mL)